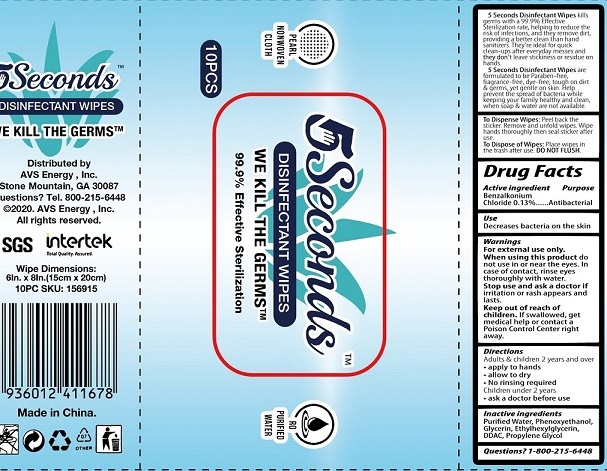 DRUG LABEL: 5 Seconds Disinfectant Wipes
NDC: 77909-004 | Form: CLOTH
Manufacturer: Zhejiang Huihao Daily Products Co.,Ltd
Category: otc | Type: HUMAN OTC DRUG LABEL
Date: 20200616

ACTIVE INGREDIENTS: BENZALKONIUM CHLORIDE 0.13 g/100 g
INACTIVE INGREDIENTS: water; GLYCERIN; PHENOXYETHANOL; ETHYLHEXYLGLYCERIN; PROPYLENE GLYCOL

Antibacterial Wipes

Active Ingredient

BENZALKONIUM CHLORIDE 0.13%

Purpose

Antibacterial

USES

Decrease bacteria on skin

Warnings

For external use only.
When using this product, do not use in or near the eyes. In case of contact, rinse eyes thoroughly with water.
Stop use and ask a doctor If irritation or rash appears and lasts.

KEEP OUT OF REACH OF CHILDREN

If swallowed, get medical help or contact a Poison Contrl Center right away.

Inactive ingredients

Purified Water, Phenoxyethanol, Glycerin, Ethylhexylglycerin, DDAC, Propylene Glycol